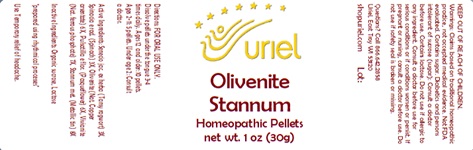 DRUG LABEL: Olivenite Stannum
NDC: 48951-7087 | Form: PELLET
Manufacturer: Uriel Pharmacy Inc.
Category: homeopathic | Type: HUMAN OTC DRUG LABEL
Date: 20240112

ACTIVE INGREDIENTS: JACOBAEA VULGARIS 3 [hp_X]/1 1; SPINACIA OLERACEA ROOT 3 [hp_X]/1 1; CUPRIC ARSENATE 6 [hp_X]/1 1; PULSATILLA VULGARIS 6 [hp_X]/1 1; FERROSOFERRIC PHOSPHATE 7 [hp_X]/1 1; TIN 8 [hp_X]/1 1
INACTIVE INGREDIENTS: SUCROSE; LACTOSE, UNSPECIFIED FORM

Olivenite Stannum

INDICATIONS AND USAGE

Directions: FOR ORAL USE ONLY.

DOSAGE AND ADMINISTRATION

Dissolve pellets under the tongue 3-4 times daily. Ages 12 and older: 10 pellets. Ages 2-11: 5 pellets. Under age 2: Consult a doctor.

ACTIVE INGREDIENT

Active Ingredients: Senecio jac. ex herba (Tansy ragwort) 3X, Spinacia e rad. (Spinach) 3X, Olivenite (Nat. Copper arsentate) 6X, Pulsatilla e flor. (Pasqueflower) 6X, Vivianite (Nat. ferrous phosphate) 7X, Stannum met. (Metallic tin) 8X

Inactive Ingredients: Organic sucrose, Lactose

"prepared using rhythmical processes"

PURPOSE

Use: Temporary relief of headache.

KEEP OUT OF REACH OF CHILDREN.

WARNINGS

Warnings: Claims based on traditional homeopathic practice, not accepted medical evidence. Not FDA evaluated. Contains sugar. Diabetics and persons intolerant of sucrose (sugar): Consult a doctor before use. Contains lactose. Do not use if allergic to any ingredient. Consult a doctor before use for serious conditions or if conditions worsen or persist. If pregnant or nursing, consult a doctor before use. Do not use if safety seal is broken or missing.

QUESTIONS

Questions? Call 866.642.2858 Uriel, East Troy, WI 53120 shopuriel.com